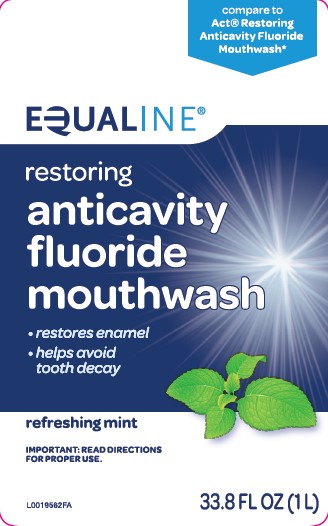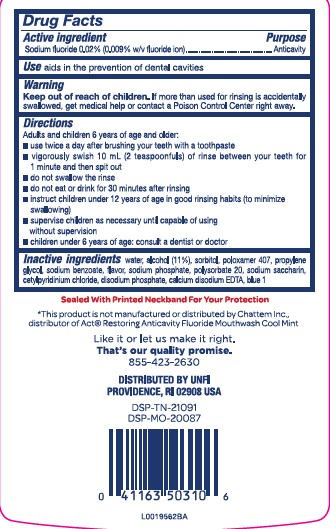 DRUG LABEL: Anticavity
NDC: 41163-581 | Form: MOUTHWASH
Manufacturer: United Natural Foods, Inc. dba UNFI
Category: otc | Type: HUMAN OTC DRUG LABEL
Date: 20260217

ACTIVE INGREDIENTS: SODIUM FLUORIDE 0.2 mg/1 mL
INACTIVE INGREDIENTS: WATER; ALCOHOL; SORBITOL; POLOXAMER 407; PROPYLENE GLYCOL; SODIUM BENZOATE; SODIUM PHOSPHATE; POLYSORBATE 20; SACCHARIN SODIUM; CETYLPYRIDINIUM CHLORIDE; SODIUM PHOSPHATE, DIBASIC, ANHYDROUS; EDETATE CALCIUM DISODIUM ANHYDROUS; FD&C BLUE NO. 1

Equaline 581.000/581AC
Restoring Anticavity Fluoride Mouthwash

Active ingredient

Sodium fluoride 0.02% (0.009% w/v fluoride ion)

Purpose

Anticavity

Use

Aids in the prevention of dental cavities

Warnings

for this product

Keep out of reach of children.

If more than used for rinsing is accidentally swallowed, get medical help or contact a Poison Control Center right away.

Directions

Adults and children 6 years of age and older:

- use twice a day after brushing your teeth with a toothpaste
- vigorously swish 10 mL (2 teaspoonfuls) of rinse between your teeth for 1 minute and then spit out
- do not swallow the rinse
- do not eat or drink for 30 minutes after rinsing
- instruct children under 12 years of age in good rinsing habits (to minimize swallowing)
- supervise children as necessary until capable of using without supervision
- children under 6 years of age: consult a dentist or doctor

Inactive ingredients

water, alcohol (11%), sorbitol, poloxamer 407, propylene glycol, sodium benzoate, flavor, sodium phosphate, polysorbate 20, sodium saccharin, cetylpyridinium chloride, disodium phosphate, calcium disodium EDTA, blue 1

Tamper Evident Statement

Sealed With Printed Neckband For Your Protection

Disclaimer

*This product is not manufactured or distributed by Chattem Inc., distributor of Act Restoring Anticavity Mouthwash Cool Mint

Adverse reaction

Like it or let us make it right.

That is our quality promise.

855-423-2630

DISTRIBUTED BY UNFI

PROVIDENCE, RI 02908 USA

DSP-TN-21091

DSP-MO-20087

Principal panel display

compare to Act®Restoring Anticavity Fluoride Mouthwash*

EQUALINE®

restoring

anticavity

fluoride

mouthwash

- restores enamel
- helps avoid tooth decay

refreshing mint

IMPORTANT: READ DIRECTIONS FOR PROPER USE

33.8 FL OZ (1.05 QT) 1 L